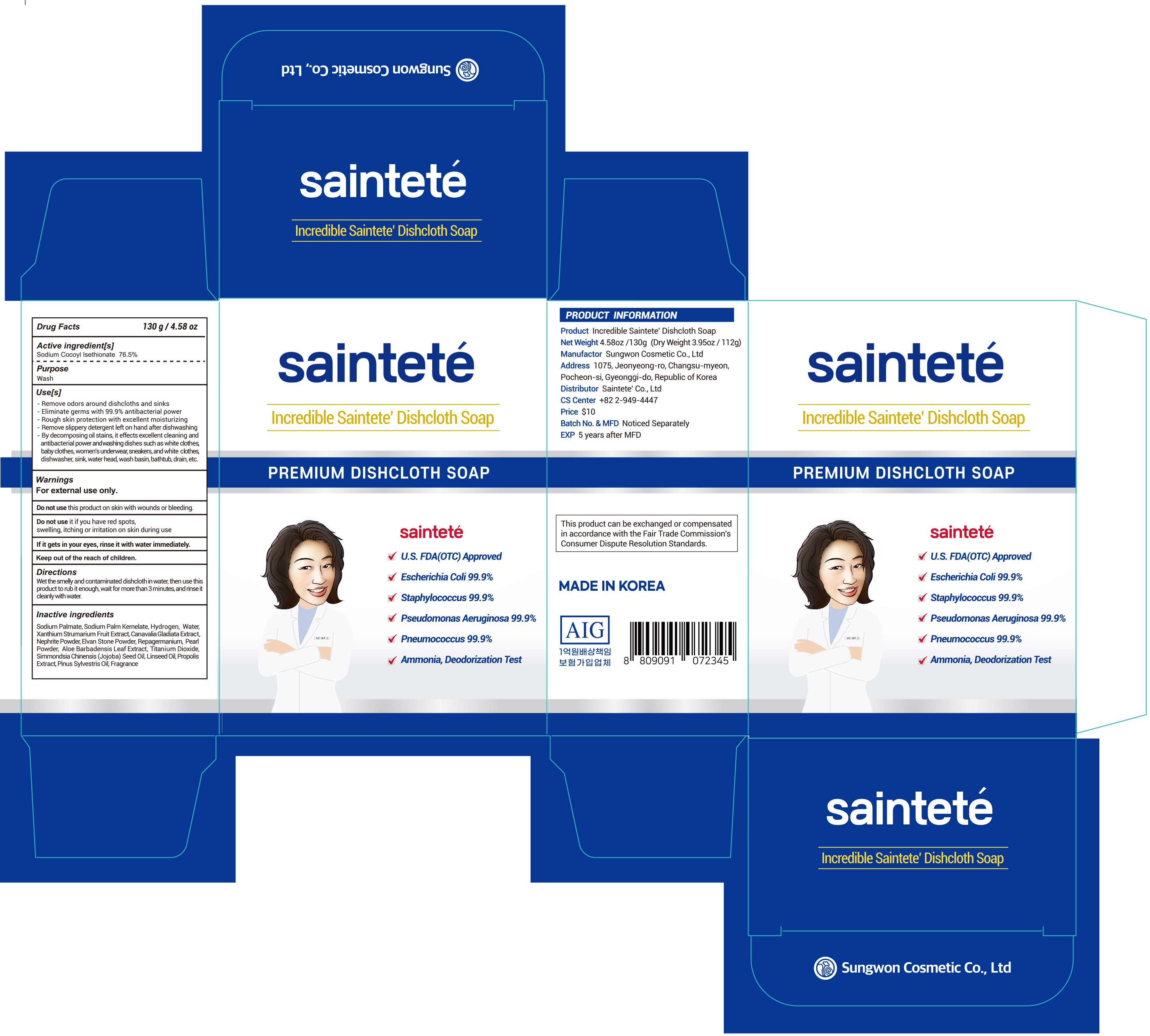 DRUG LABEL: Incredible Saintete DishclothSoap
NDC: 74721-0090 | Form: SOAP
Manufacturer: S-ONE PHARMACEUTICAL INC
Category: otc | Type: HUMAN OTC DRUG LABEL
Date: 20230125

ACTIVE INGREDIENTS: SODIUM COCOYL ISETHIONATE 76.5 g/100 g
INACTIVE INGREDIENTS: SODIUM PALMATE; HYDROGEN; XANTHIUM STRUMARIUM FRUIT; PROPAGERMANIUM; ALOE VERA LEAF; PEARL (HYRIOPSIS CUMINGII); TITANIUM DIOXIDE; LINSEED OIL; WATER; SODIUM PALM KERNELATE; JOJOBA OIL; PROPOLIS WAX; PINE NEEDLE OIL (PINUS SYLVESTRIS)

74721-0090 Incredible Saintete’ Dishcloth Soap

Active ingredient

Sodium Cocoyl Isethionate 76.5%

Purpose

Wash

Use[s]

- Remove odors around dishcloths and sinks
- Eliminate germs with 99.9% antibacterial power
- Rough skin protection with excellent moisturizing
- Remove slippery detergent left on hand after dishwashing
- By decomposing oil stains, it effects excellent cleaning and antibacterial power and washing dishes such as white clothes, baby clothes, women's underwear, sneakers, and white clothes, dishwasher, sink, water head, wash basin, bathtub, drain, etc.

Warnings

For external use only.

Do not use this product on skin with wounds or bleeding.

Do not use it if you have red spots, swelling, itching or irritation on skin during use.

Stop use

If it gets in your eyes, rinse it with water immediately.

Keep out of reach of children.

DIRECTIONS FOR USE

Wet the smelly and contaminated dishcloth in water, then use this product to rub it enough, wait for more than 3 minutes, and rinse it cleanly with water.

Inacitve ingredients

Sodium Palmate, Sodium Palm Kernelate, Hydrogen, Water, Xanthium Strumarium Fruit Extract, Canavalia Gladiata Extract, Nephrite Powder, Elvan Stone Powder, Repagermanium, Pearl Powder, Aloe Barbadensis Leaf Extract, Titanium Dioxide, Simmondsia Chinensis (Jojoba) Seed Oil, Linseed Oil, Propolis Extract, Pinus Sylvestris Oil, Fragranc